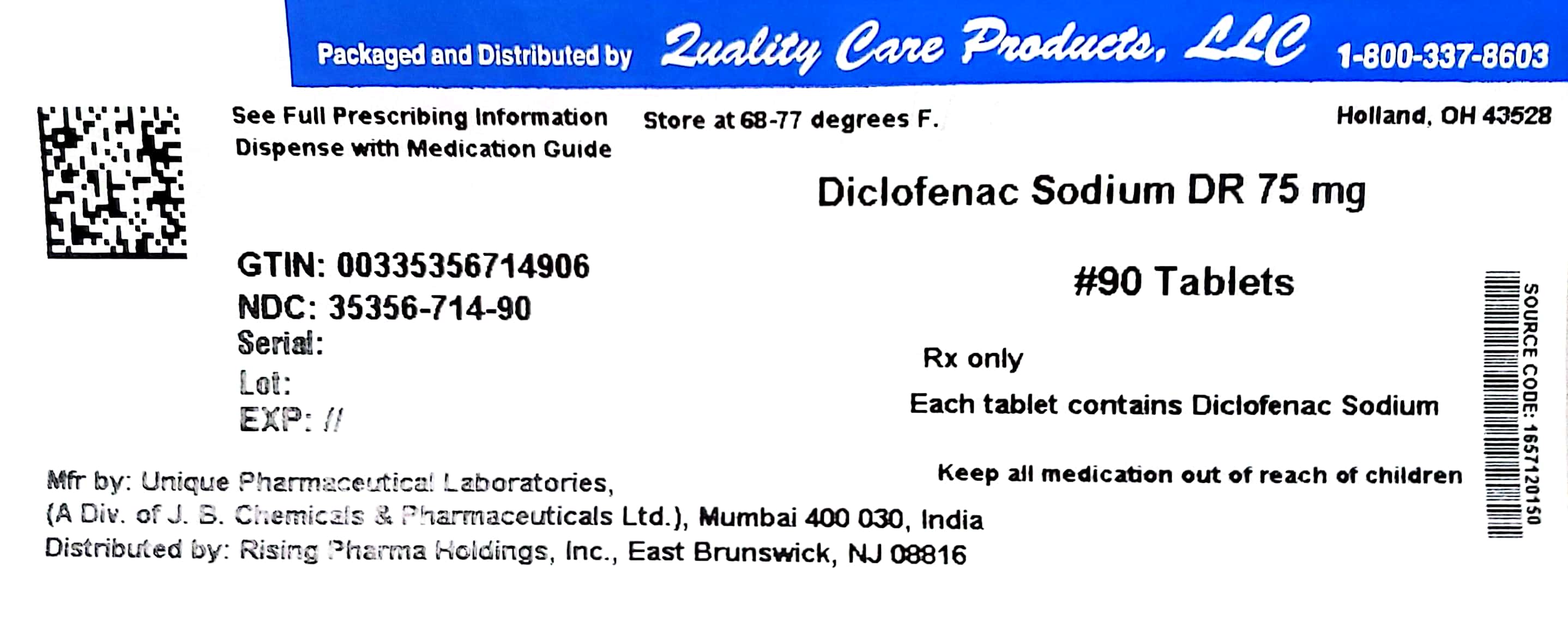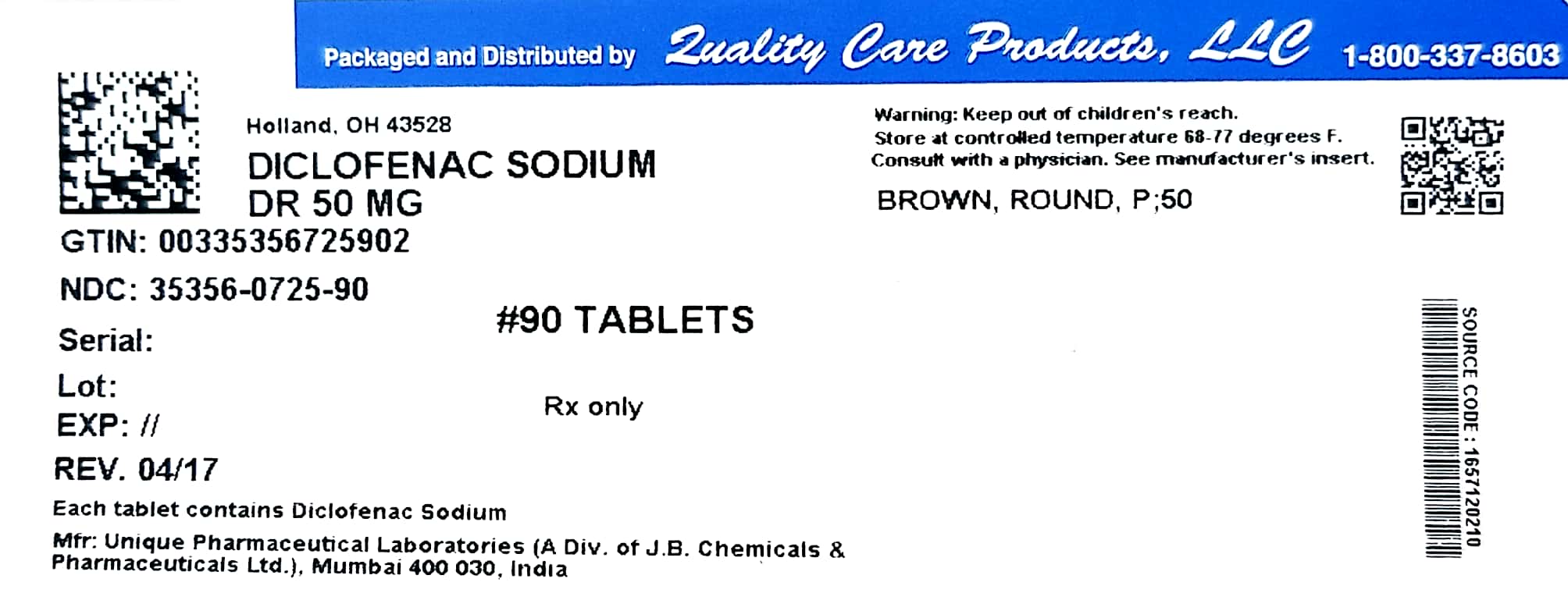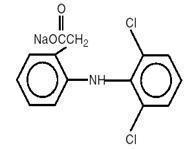 DRUG LABEL: Diclofenac Sodium
NDC: 35356-714 | Form: TABLET, DELAYED RELEASE
Manufacturer: Quality Care Products LLC
Category: prescription | Type: HUMAN PRESCRIPTION DRUG LABEL
Date: 20241211

ACTIVE INGREDIENTS: Diclofenac Sodium 75 mg/1 1
INACTIVE INGREDIENTS: LACTOSE MONOHYDRATE; CELLULOSE, MICROCRYSTALLINE; croscarmellose sodium; POVIDONE; talc; magnesium stearate; METHACRYLIC ACID - ETHYL ACRYLATE COPOLYMER (1:1) TYPE A; POLYETHYLENE GLYCOL, UNSPECIFIED; Titanium dioxide; hypromelloses; FERRIC OXIDE RED; FERRIC OXIDE YELLOW; water

Diclofenac Sodium Delayed-release Tablets USP, 25 mg, 50 mg and 75 mg

Rx only

Prescribing information

BOXED WARNING

Cardiovascular Risk

- NSAIDs may cause an increased risk of serious cardiovascular thrombotic events, myocardial infarction, and stroke, which can be fatal. This risk may increase with duration of use. Patients with cardiovascular disease or risk factors for cardiovascular disease may be at greater risk. (See WARNINGS.)
- Diclofenac sodium delayed-release tablets are contraindicated for the treatment of perioperative pain in the setting of coronary artery bypass graft (CABG) surgery (see WARNINGS).

Gastrointestinal Risk

- NSAIDs cause an increased risk of serious gastrointestinal adverse events including inflammation, bleeding, ulceration, and perforation of the stomach or intestines, which can be fatal. These events can occur at any time during use and without warning symptoms. Elderly patients are at greater risk for serious gastrointestinal events. (See WARNINGS).

DESCRIPTION

Diclofenac sodium delayed-release tablets are a benzene-acetic acid derivative. Diclofenac sodium delayed-release tablets are available as delayed-release tablets of 75 mg for oral administration. The chemical name is 2-[(2,6-dichlorophenyl)amino] benzeneacetic acid, monosodium salt. The molecular weight is 318.14. Its molecular formula is C14H10Cl2NNaO2, and it has the following structural formula

The inactive ingredients in Diclofenac sodium delayed-release tablets include: lactose (monohydrate), microcrystalline cellulose, croscarmellose sodium, povidone, talc, magnesium stearate, methacrylic acid copolymer, polyethylene glycol, opadry brown (Titanium dioxide, hypromellose, polyethylene glycol, iron oxide red, iron oxide yellow) and purified water.

CLINICAL PHARMACOLOGY

Pharmacodynamics

Diclofenac sodium delayed-release tablets, are a nonsteroidal anti-inflammatory drug (NSAID) that exhibits anti-inflammatory, analgesic, and antipyretic activities in animal models. The mechanism of action of diclofenac sodium delayed-release tablets, like that of other NSAIDs, is not completely understood but may be related to prostaglandin synthetase inhibition.

Pharmacokinetics

Absorption

Diclofenac is 100% absorbed after oral administration compared to IV administration as measured by urine recovery. However, due to first-pass metabolism, only about 50% of the absorbed dose is systemically available (see Table 1). Food has no significant effect on the extent of diclofenac absorption. However, there is usually a delay in the onset of absorption of 1 to 4.5 hours and a reduction in peak plasma levels of <20%.

Table 1. Pharmacokinetic Parameters for Diclofenac
 | Normal Healthy Adults (20-48 yrs.)
PK Parameter | Mean | Coefficient of Mean Variation (%)
Absolute Bioavailability (%) [N = 7] | 55 | 40
Tmax (hr) [N = 56] | 2.3 | 69
Oral Clearance (CL/F; mL/min) [N = 56] | 582 | 23
Renal Clearance (% unchanged drug in urine) [N = 7] | <1 | –
Apparent Volume of Distribution (V/F; L/kg) [N = 56] | 1.4 | 58
Terminal Half-life (hr) [N = 56] | 2.3 | 48

Distribution

The apparent volume of distribution (V/F) of diclofenac sodium is 1.4 L/kg.

Diclofenac is more than 99% bound to human serum proteins, primarily to albumin. Serum protein binding is constant over the concentration range (0.15-105 μg/mL) achieved with recommended doses.

Diclofenac diffuses into and out of the synovial fluid. Diffusion into the joint occurs when plasma levels are higher than those in the synovial fluid, after which the process reverses and synovial fluid levels are higher than plasma levels. It is not known whether diffusion into the joint plays a role in the effectiveness of diclofenac.

Metabolism

Five Diclofenac metabolites have been identified in human plasma and urine. The metabolites include 4'-hydroxy-, 5-hydroxy-, 3'-hydroxy-, 4',5-dihydroxy- and 3'-hydroxy-4'-methoxy-Diclofenac. The major Diclofenac metabolite, 4'-hydroxy-Diclofenac, has very weak pharmacologic activity. The formation of 4’-hydroxy- Diclofenac is primarily mediated by CPY2C9. Both Diclofenac and its oxidative metabolites undergo glucuronidation or sulfation followed by biliary excretion. Acylglucuronidation mediated by UGT2B7 and oxidation mediated by CPY2C8 may also play a role in Diclofenac metabolism. CYP3A4 is responsible for the formation of minor metabolites, 5-hydroxy- and 3’-hydroxy-Diclofenac. In patients with renal dysfunction, peak concentrations of metabolites 4'-hydroxy- and 5-hydroxy-Diclofenac were approximately 50% and 4% of the parent compound after single oral dosing compared to 27% and 1% in normal healthy subjects.

Excretion

Diclofenac is eliminated through metabolism and subsequent urinary and biliary excretion of the glucuronide and the sulfate conjugates of the metabolites. Little or no free unchanged diclofenac is excreted in the urine. Approximately 65% of the dose is excreted in the urine and approximately 35% in the bile as conjugates of unchanged diclofenac plus metabolites. Because renal elimination is not a significant pathway of elimination for unchanged diclofenac, dosing adjustment in patients with mild to moderate renal dysfunction is not necessary. The terminal half-life of unchanged diclofenac is approximately 2 hours.

Drug Interactions

When co-administered with voriconazole (inhibitor of CYP2C9, 2C19 and 3A4 enzyme), the Cmax and AUC of Diclofenac increased by 114% and 78%, respectively (see PRECAUTIONS, Drug Interactions).

Special Populations

Pediatric: The pharmacokinetics of diclofenac sodium delayed-release tablets has not been investigated in pediatric patients.

Race: Pharmacokinetics differences due to race have not been identified.

Hepatic Insufficiency: Hepatic metabolism accounts for almost 100% of diclofenac sodium delayed-release tablets elimination, so patients with hepatic disease may require reduced doses of diclofenac sodium delayed-release tablets compared to patients with normal hepatic function.

Renal Insufficiency: Diclofenac pharmacokinetics has been investigated in subjects with renal insufficiency. No differences in the pharmacokinetics of diclofenac have been detected in studies of patients with renal impairment. In patients with renal impairment (inulin clearance 60-90, 30-60, and <30 mL/min; N=6 in each group), AUC values and elimination rate were comparable to those in healthy subjects.

INDICATIONS AND USAGE

Carefully consider the potential benefits and risks of diclofenac sodium delayed-release tablets and other treatment options before deciding to use diclofenac sodium delayed-release tablets. Use the lowest effective dose for the shortest duration consistent with individual patient treatment goals (see WARNINGS).

Diclofenac sodium delayed-release tablets, are indicated:

- For relief of signs and symptoms of osteoarthritis
- For relief of signs and symptoms of rheumatoid arthritis
- For acute or long-term use in the relief of signs and symptoms of ankylosing spondylitis

CONTRAINDICATIONS

Diclofenac sodium delayed-release tablets are contraindicated in patients with known hypersensitivity to diclofenac.

Diclofenac sodium delayed-release tablets should not be given to patients who have experienced asthma, urticaria, or other allergic-type reactions after taking aspirin or other NSAIDs. Severe, rarely fatal, anaphylactic-like reactions to NSAIDs have been reported in such patients (see WARNINGS, Anaphylactoid Reactions, and PRECAUTIONS, Preexisting Asthma).

Diclofenac sodium delayed-release tablets are contraindicated for the treatment of peri-operative pain in the setting of coronary artery bypass graft (CABG) surgery (see WARNINGS).

WARNINGS

Gastrointestinal (GI) Effects – Risk of GI Ulceration, Bleeding, and Perforation

NSAIDs, including diclofenac sodium delayed-release tablets, can cause serious gastrointestinal (GI) adverse events including inflammation, bleeding, ulceration, and perforation of the stomach, small intestine, or large intestine, which can be fatal. These serious adverse events can occur at any time, with or without warning symptoms, in patients treated with NSAIDs. Only one in five patients, who develop a serious upper GI adverse event on NSAID therapy, is symptomatic. Upper GI ulcers, gross bleeding, or perforation caused by NSAIDs occur in approximately 1% of patients treated for 3-6 months, and in about 2-4% of patients treated for one year. These trends continue with longer duration of use, increasing the likelihood of developing a serious GI event at some time during the course of therapy. However, even short-term therapy is not without risk.

NSAIDs should be prescribed with extreme caution in those with a prior history of ulcer disease or gastrointestinal bleeding. Patients with a prior history of peptic ulcer disease and/or gastrointestinal bleeding who use NSAIDs have a greater than 10-fold increased risk for developing a GI bleed compared to patients with neither of these risk factors. Other factors that increase the risk for GI bleeding in patients treated with NSAIDs include concomitant use of oral corticosteroids or anticoagulants, longer duration of NSAID therapy, smoking, use of alcohol, older age, and poor general health status. Most spontaneous reports of fatal GI events are in elderly or debilitated patients and therefore, special care should be taken in treating this population.

To minimize the potential risk for an adverse GI event in patients treated with an NSAID, the lowest effective dose should be used for the shortest possible duration. Patients and physicians should remain alert for signs and symptoms of GI ulceration and bleeding during NSAID therapy and promptly initiate additional evaluation and treatment if a serious GI adverse event is suspected. This should include discontinuation of the NSAID until a serious GI adverse event is ruled out. For high risk patients, alternate therapies that do not involve NSAIDs should be considered.

Renal Effects

Caution should be used when initiating treatment with diclofenac sodium delayed-release tablets in patients with considerable dehydration.

Long-term administration of NSAIDs has resulted in renal papillary necrosis and other renal injury. Renal toxicity has also been seen in patients in whom renal prostaglandins have a compensatory role in the maintenance of renal perfusion. In these patients, administration of a nonsteroidal anti-inflammatory drug may cause a dose-dependent reduction in prostaglandin formation and, secondarily, in renal blood flow, which may precipitate overt renal decompensation. Patients at greatest risk of this reaction are those with impaired renal function, heart failure, liver dysfunction, those taking diuretics and ACE inhibitors, and the elderly. Discontinuation of NSAID therapy is usually followed by recovery to the pretreatment state.

Advanced Renal Disease

No information is available from controlled clinical studies regarding the use of diclofenac sodium delayed-release tablets in patients with advanced renal disease. Therefore, treatment with diclofenac sodium delayed-release tablets are not recommended in these patients with advanced renal disease. If diclofenac sodium delayed-release tablets therapy must be initiated, close monitoring of the patient’s renal function is advisable.

Hepatic Effects

Elevations of one or more liver tests may occur during therapy with Diclofenac delayed-release tablets. These laboratory abnormalities may progress, may remain unchanged, or may be transient with continued therapy. Borderline elevations (i.e., less than 3 times the ULN [ULN = the upper limit of the normal range]) or greater elevations of transaminases occurred in about 15% of Diclofenac-treated patients. Of the markers of hepatic function, ALT (SGPT) is recommended for the monitoring of liver injury.

In clinical trials, meaningful elevations (i.e., more than 3 times the ULN) of AST (GOT) (ALT was not measured in all studies) occurred in about 2% of approximately 5,700 patients at some time during Diclofenac treatment. In a large, open-label, controlled trial of 3,700 patients treated for 2-6 months, patients were monitored first at 8 weeks and 1,200 patients were monitored again at 24 weeks. Meaningful elevations of ALT and/or AST occurred in about 4% of patients and included marked elevations (i.e., more than 8 times the ULN) in about 1% of the 3,700 patients. In that open-label study, a higher incidence of borderline (less than 3 times the ULN), moderate (3-8 times the ULN), and marked (>8 times the ULN) elevations of ALT or AST was observed in patients receiving Diclofenac when compared to other NSAIDs. Elevations in transaminases were seen more frequently in patients with osteoarthritis than in those with rheumatoid arthritis.

Almost all meaningful elevations in transaminases were detected before patients became symptomatic. Abnormal tests occurred during the first 2 months of therapy with Diclofenac in 42 of the 51 patients in all trials who developed marked transaminase elevations.

In postmarketing reports, cases of drug-induced hepatotoxicity have been reported in the first month, and in some cases, the firth 2 months of therapy, but can occur at any time during treatment with Diclofenac. Postmarketing surveillance has reported cases of severe hepatic reactions, including liver necrosis, jaundice, fulminant hepatitis with and without jaundice, and liver failure. Some of these reported cases resulted in fatalities or liver transplantation.

Physicians should measure transaminases periodically in patients receiving long-term therapy with Diclofenac, because severe hepatotoxicity may develop without a prodrome of distinguishing symptoms. The optimum times for making the first and subsequent transaminase measurements are not known. Based on clinical trial data and postmarketing experiences, transaminases should be monitored within 4 to 8 weeks after initiating treatment with Diclofenac. However, severe hepatic reaction can occur at any time during treatment with Diclofenac.

If abnormal liver tests persist or worsen, if clinical signs and/or symptoms consistent with liver disease develop, or if systemic manifestations occur (e.g., eosinophilia, rash, abdominal pain, diarrhea, dark urine, etc.), Diclofenac sodium delayed-release tablets should be discontinued immediately.

To minimize the possibility that hepatic injury will become severe between transaminase measurements, physicians should inform patients of the warning signs and symptoms of hepatotoxicity (e.g., nausea, fatigue, lethargy, diarrhea, pruritus, jaundice, right upper quadrant tenderness, and “flu-like” symptoms), and the appropriate action patients should take if these signs and symptoms appear.

To minimize the potential risk for an adverse liver related event in patients treated with Diclofenac sodium delayed-release tablets, the lowest effective dose should be used for the shortest duration possible. Caution should be exercised in prescribing Diclofenac sodium delayed-release tablets with concomitant drugs that are known to be potentially hepatotoxic (e.g., antibiotics, anti-epileptics).

Anaphylactic Reactions

As with other NSAIDs, anaphylactic reactions may occur both in patients with the aspirin traid and in patients without known sensitivity to NSAIDs or known prior exposure to Diclofenac Sodium Delayed-release Tablets. Diclofenac Sodium Delayed-release Tablets should not be given to patients with the aspirin triad. This symptom complex typically occurs in asthmatic patients who experience rhinitis with or without nasal polyps, or who exhibit severe, potentially fatal bronchospasm after taking aspirin or other NSAIDs (see CONTRAINDICATIONS and PRECAUTIONS, Preexisting Asthma.) Anaphylaxis-type reactions have been reported with NSAID products, including with Diclofenac products, such as Diclofenac Sodium Delayed-Release Tablet. Emergency help should be sought in cases where an anaphylactoid reaction occurs.

Skin Reactions

NSAIDs, including diclofenac sodium delayed-release tablets, can cause serious skin adverse events such as exfoliative dermatitis, Stevens-Johnson Syndrome (SJS), and toxic epidermal necrolysis (TEN), which can be fatal. These serious events may occur without warning. Patients should be informed about the signs and symptoms of serious skin manifestations and use of the drug should be discontinued at the first appearance of skin rash or any other sign of hypersensitivity.

Pregnancy

In late pregnancy, as with other NSAIDs, diclofenac sodium delayed-release tablets should be avoided because it may cause premature closure of the ductus arteriosus.

ADVERSE REACTIONS

In patients taking diclofenac sodium delayed-release tablets, or other NSAIDs, the most frequently reported adverse experiences occurring in approximately 1%-10% of patients are:

Gastrointestinal experiences including: abdominal pain, constipation, diarrhea, dyspepsia, flatulence, gross bleeding/perforation, heartburn, nausea, GI ulcers (gastric/duodenal) and vomiting.

Abnormal renal function, anemia, dizziness, edema, elevated liver enzymes, headaches, increased bleeding time, pruritus, rashes and tinnitus.

Additional adverse experiences reported occasionally include:

Body as a Whole: fever, infection, sepsis

Cardiovascular System: congestive heart failure, hypertension, tachycardia, syncope

Digestive System: dry mouth, esophagitis, gastric/peptic ulcers, gastritis, gastrointestinal bleeding, glossitis, hematemesis, hepatitis, jaundice

Hemic and Lymphatic System: ecchymosis, eosinophilia, leukopenia, melena, purpura, rectal bleeding, stomatitis, thrombocytopenia

Metabolic and Nutritional: weight changes

Nervous System: anxiety, asthenia, confusion, depression, dream abnormalities, drowsiness, insomnia, malaise, nervousness, paresthesia, somnolence, tremors, vertigo

Respiratory System: asthma, dyspnea

Skin and Appendages: alopecia, photosensitivity, sweating increased

Special Senses: blurred vision

Urogenital System: cystitis, dysuria, hematuria, interstitial nephritis, oliguria/ polyuria, proteinuria, renal failure

Other adverse reactions, which occur rarely are:

Body as a Whole: anaphylactic reactions, appetite changes, death

Cardiovascular System: arrhythmia, hypotension, myocardial infarction, palpitations, vasculitis

Digestive System: colitis, eructation, fulminant hepatitis with and without jaundice, liver failure, liver necrosis, pancreatitis

Hemic and Lymphatic System: agranulocytosis, hemolytic anemia, aplastic anemia, lymphadenopathy, pancytopenia

Metabolic and Nutritional: hyperglycemia

Nervous System: convulsions, coma, hallucinations, meningitis

Respiratory System: respiratory depression, pneumonia

Skin and Appendages: angioedema, toxic epidermal necrolysis, erythema multiforme, exfoliative dermatitis, Stevens-Johnson syndrome, urticaria

Special Senses: conjunctivitis, hearing impairment

OVERDOSAGE

Symptoms following acute NSAID overdoses are usually limited to lethargy, drowsiness, nausea, vomiting, and epigastric pain, which are generally reversible with supportive care. Gastrointestinal bleeding can occur. Hypertension, acute renal failure, respiratory depression and coma may occur, but are rare. Anaphylactoid reactions have been reported with therapeutic ingestion of NSAIDs, and may occur following an overdose.

Patients should be managed by symptomatic and supportive care following a NSAID overdose. There are no specific antidotes. Emesis and/or activated charcoal (60 to 100 g in adults, 1 to 2 g/kg in children) and/or osmotic cathartic may be indicated in patients seen within 4 hours of ingestion with symptoms or following a large overdose (5 to 10 times the usual dose). Forced diuresis, alkalinization of urine, hemodialysis, or hemoperfusion may not be useful due to high protein binding.

DOSAGE AND ADMINISTRATION

Carefully consider the potential benefits and risks of diclofenac sodium delayed-release tablets and other treatment options before deciding to use diclofenac sodium delayed-release tablets. Use the lowest effective dose for the shortest duration consistent with individual patient treatment goals (see WARNINGS).

After observing the response to initial therapy with diclofenac sodium delayed-release tablets, the dose and frequency should be adjusted to suit an individual patient’s needs.

For the relief of osteoarthritis, the recommended dosage is 100-150 mg/day in divided doses (50 mg b.i.d. or t.i.d., or 75 mg b.i.d.).

For the relief of rheumatoid arthritis, the recommended dosage is 150-200 mg/day in divided doses (50 mg t.i.d. or q.i.d., or 75 mg b.i.d.).

For the relief of ankylosing spondylitis, the recommended dosage is 100-125 mg/day, administered as 25 mg q.i.d., with an extra 25-mg dose at bedtime if necessary.

Different formulations of diclofenac (diclofenac sodium enteric-coated tablets; diclofenac sodium extended-release tablets, diclofenac potassium immediate-release tablets) are not necessarily bioequivalent even if the milligram strength is the same.

HOW SUPPLIED

35356-714-14

35356-714-20

35356-714-28

35356-714-30

35356-714-60

35356-714-90

35356-725-30

35356-725-60

35356-725-90

MEDICATION GUIDE

MEDICATION GUIDE for Non-Steroidal Anti-Inflammatory Drugs (NSAIDs)
(See the end of this Medication Guide for a list of prescription NSAID medicines.)

What is the most important information I should know about medicines called Non-Steroidal Anti-Inflammatory Drugs (NSAIDs)?

NSAID medicines may increase the chance of a heart attack or stroke that can lead to death. This chance increases:

- with longer use of NSAID medicines
- in people who have heart disease

NSAID medicines should never be used right before or after a heart surgery called a “coronary artery bypass graft (CABG).”

NSAID medicines can cause ulcers and bleeding in the stomach and intestines at any time during treatment. Ulcers and bleeding:

- can happen without warning symptoms
- may cause death

The chance of a person getting an ulcer or bleeding increases with:

- taking medicines called “corticosteroids” and “anticoagulants”
- longer use
- smoking
- drinking alcohol
- older age
- having poor health

NSAID medicines should only be used:

- exactly as prescribed
- at the lowest dose possible for your treatment
- for the shortest time needed

What are Non-Steroidal Anti-Inflammatory Drugs (NSAIDs)?

NSAID medicines are used to treat pain and redness, swelling, and heat (inflammation) from medical conditions such as:

- different types of arthritis
- menstrual cramps and other types of short-term pain

Who should not take a Non-Steroidal Anti-Inflammatory Drug (NSAID)?

Do not take an NSAID medicine:

- if you had an asthma attack, hives, or other allergic reaction with aspirin or any other NSAID medicine
- for pain right before or after heart bypass surgery

Tell your healthcare provider:

- about all your medical conditions.
- about all of the medicines you take. NSAIDs and some other medicines can interact with each other and cause serious side effects. Keep a list of your medicines to show to your healthcare provider and pharmacist.
- if you are pregnant. NSAID medicines should not be used by pregnant women late in their pregnancy.
- if you are breastfeeding. Talk to your doctor.

What are the possible side effects of Non-Steroidal Anti-Inflammatory Drugs (NSAIDs)?

Serious side effects include:

- heart attack
- stroke
- high blood pressure
- heart failure from body swelling (fluid retention)
- kidney problems including kidney failure
- bleeding and ulcers in the stomach and intestine
- low red blood cells (anemia)
- life-threatening skin reactions
- life-threatening allergic reactions
- liver problems including liver failure
- asthma attacks in people who have asthma

Other side effects include:

- stomach pain
- constipation
- diarrhea
- gas
- heartburn
- nausea
- vomiting
- dizziness

Get emergency help right away if you have any of the following symptoms:

- shortness of breath or trouble breathing
- chest pain
- weakness in one part or side of your body
- slurred speech
- swelling of the face or throat

Stop your NSAID medicine and call your healthcare provider right away if you have any of the following symptoms:

- nausea
- more tired or weaker than usual
- itching
- your skin or eyes look yellow
- stomach pain
- flu-like symptoms
- vomit blood
- there is blood in your bowel movement or it is black and sticky like tar
- unusual weight gain
- skin rash or blisters with fever
- swelling of the arms and legs, hands and feet

These are not all the side effects with NSAID medicines. Talk to your healthcare provider or pharmacist for more information about NSAID medicines. Call your doctor for medical advice about side effects. You may report side effects to FDA at 1-800-FDA-1088.

Other information about Non-Steroidal Anti-Inflammatory Drugs (NSAIDs)

- Aspirin is an NSAID medicine but it does not increase the chance of a heart attack. Aspirin can cause bleeding in the brain, stomach, and intestines. Aspirin can also cause ulcers in the stomach and intestines.
- Some of these NSAID medicines are sold in lower doses without a prescription (over-the-counter). Talk to your healthcare provider before using over-the-counter NSAIDs for more than 10 days.

NSAID medicines that need a prescription

Generic Name | Tradename
Celecoxib | Celebrex®
Diclofenac | Cataflam®, Voltaren®, Arthrotec™ (combined with misoprostol)
Diflunisal | Dolobid®
Etodolac | Lodine®, Lodine® XL
Fenoprofen | Nalfon®, Nalfon ®200
Flurbiprofen | Ansaid®
Ibuprofen | Motrin®, Tab-Profen®, Vicoprofen®* (combined with hydrocodone), Combunox™ (combined with oxycodone)
Indomethacin | Indocin®, Indocin ® SR, Indo-Lemmon™, Indomethagan™
Ketoprofen | Oruvail®
Ketorolac | Toradol®
Mefenamic Acid | Ponstel®
Meloxicam | Mobic®
Nabumetone | Relafen®
Naproxen | Naprosyn®, Anaprox®, Anaprox ®DS, EC-Naproxyn™, Naprelan®, Naprapac® (copackaged with lansoprazole)
Oxaprozin | Daypro®
Piroxicam | Feldene®
Sulindac | Clinoril®
Tolmetin | Tolectin®, Tolectin DS®, Tolectin® 600
*Vicoprofen contains the same dose of ibuprofen as over-the-counter (OTC) NSAIDs, and is usually used for less than 10 days to treat pain. The OTC NSAID label warns that long term continuous use may increase the risk of heart attack or stroke.

All registered trademarks in this document are the property of their respective owners.

This Medication Guide has been approved by the U.S. Food and Drug Administration.

Manufactured by:

UNIQUE PHARMACEUTICAL LABORATORIES.
(A Div. of J. B. Chemicals & Pharmaceuticals Ltd.)
Mumbai 400 030, India.

Marketed by:

PACK Pharmaceuticals, LLC
Buffalo Grove, IL 60089